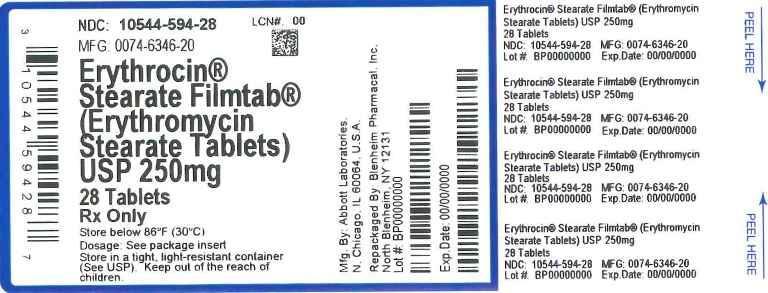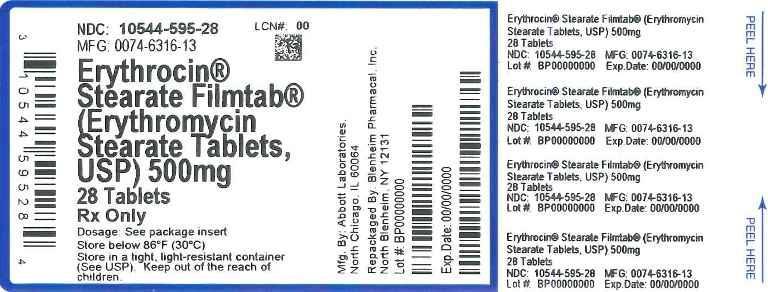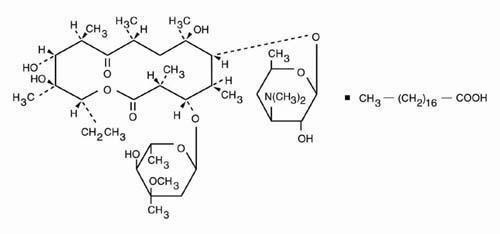 DRUG LABEL: Erythrocin Stearate
NDC: 10544-594 | Form: TABLET, FILM COATED
Manufacturer: Blenheim Pharmacal, Inc.
Category: prescription | Type: HUMAN PRESCRIPTION DRUG LABEL
Date: 20150731

ACTIVE INGREDIENTS: ERYTHROMYCIN STEARATE 250 mg/1 1
INACTIVE INGREDIENTS: STARCH, CORN; D&C RED NO. 7; POLACRILIN POTASSIUM; POVIDONES; CARBOXYMETHYLCELLULOSE SODIUM; SODIUM CITRATE; SORBIC ACID; SORBITAN MONOOLEATE; TITANIUM DIOXIDE; POLYETHYLENE GLYCOLS

ERYTHROCIN® STEARATE
(erythromycin stearate tablets, USP)
Filmtab® Tablets

To reduce the development of drug-resistant bacteria and maintain the effectiveness of ERYTHROCIN STEARATE Filmtab tablets and other antibacterial drugs, ERYTHROCIN STEARATE Filmtab tablets should be used only to treat or prevent infections that are proven or strongly suspected to be caused by bacteria.

DESCRIPTION

ERYTHROCIN STEARATE Filmtab tablets (erythromycin stearate tablets, USP) are an antibacterial product containing the stearate salt of erythromycin in a unique film coating.

Erythromycin is produced by a strain of Saccharopolyspora erythraea (formerly Streptomyces erythraeus) and belongs to the macrolide group of antibiotics. It is basic and readily forms salts with acids. Erythromycin is a white to off-white powder, slightly soluble in water, and soluble in alcohol, chloroform, and ether. Erythromycin stearate is known chemically as erythromycin octadecanoate. The molecular formula of erythromycin stearate is C37H67NO13•C18H36O2, and the molecular weight is 1018.43. The structural formula is:

Inactive Ingredients

250 mg tablet

Cellulosic polymers, corn starch, D&C Red No. 7, polacrilin potassium, polyethylene glycol, povidone, propylene glycol, sodium carboxymethylcellulose, sodium citrate, sorbic acid, sorbitan monooleate and titanium dioxide.

500 mg tablet

Cellulosic polymers, cornstarch, FD&C Red No. 3, magnesium hydroxide, polacrilin potassium, povidone, propylene glycol, sorbitan monooleate, titanium dioxide and vanillin.

CLINICAL PHARMACOLOGY

Orally administered erythromycin base and its salts are readily absorbed in the microbiologically active form. Interindividual variations in the absorption of erythromycin are, however, observed, and some patients do not achieve optimal serum levels. Erythromycin is largely bound to plasma proteins. After absorption, erythromycin diffuses readily into most body fluids. In the absence of meningeal inflammation, low concentrations are normally achieved in the spinal fluid but the passage of the drug across the blood-brain barrier increases in meningitis. Erythromycin crosses the placental barrier, but fetal plasma levels are low. The drug is excreted in human milk. Erythromycin is not removed by peritoneal dialysis or hemodialysis.

In the presence of normal hepatic function, erythromycin is concentrated in the liver and is excreted in the bile; the effect of hepatic dysfunction on biliary excretion of erythromycin is not known. After oral administration, less than 5% of the administered dose can be recovered in the active form in the urine.

Orally administered ERYTHROCIN STEARATE tablets are readily and reliably absorbed. Optimal serum levels of erythromycin are reached when the drug is taken in the fasting state or immediately before meals.

Microbiology

Erythromycin acts by inhibition of protein synthesis by binding 50 S ribosomal subunits of susceptible organisms. It does not affect nucleic acid synthesis. Antagonism has been demonstrated in vitro between erythromycin and clindamycin, lincomycin, and chloramphenicol.

Many strains of Haemophilus influenzae are resistant to erythromycin alone, but are susceptible to erythromycin and sulfonamides used concomitantly.

Staphylococci resistant to erythromycin may emerge during a course of erythromycin therapy. Erythromycin has been shown to be active against most strains of the following microorganisms, both in vitro and in clinical infections as described in the INDICATIONS AND USAGE section.

Gram-positive organisms

Corynebacterium diphtheriae

Corynebacterium minutissimum

Listeria monocytogenes

Staphylococcus aureus (resistant organisms may emerge during treatment)

Streptococcus pneumoniae

Streptococcus pyogenes

Gram-negative organisms

Bordetella pertussis

Legionella pneumophila

Neisseria gonorrhoeae

Other microorganisms

Chlamydia trachomatis

Entamoeba histolytica

Mycoplasma pneumoniae

Treponema pallidum

Ureaplasma urealyticum

The following in vitro data are available, but their clinical significance is unknown.

Erythromycin exhibits in vitro minimal inhibitory concentrations (MIC's) of 0.5 µg/mL or less against most (≥ 90%) strains of the following microorganisms; however, the safety and effectiveness of erythromycin in treating clinical infections due to these microorganisms have not been established in adequate and well-controlled clinical trials.

Gram-positive organisms

Viridans group streptococci

Gram-negative organisms

Moraxella catarrhalis

Susceptibility Tests

Dilution Techniques

Quantitative methods are used to determine antimicrobial minimum inhibitory concentrations (MIC's). These MIC's provide estimates of the susceptibility of bacteria to antimicrobial compounds. The MIC's should be determined using a standardized procedure. Standardized procedures are based on a dilution method^1 (broth or agar) or equivalent with standardized inoculum concentrations and standardized concentrations of erythromycin powder. The MIC values should be interpreted according to the following criteria:

MIC (µg/mL) | Interpretation
≤ 0.5 | Susceptible (S)
1-4 | Intermediate (I)
≥ 8 | Resistant (R)

A report of "Susceptible" indicates that the pathogen is likely to be inhibited if the antimicrobial compound in the blood reaches the concentrations usually achievable. A report of "Intermediate" indicates that the result should be considered equivocal, and, if the microorganism is not fully susceptible to alternative, clinically feasible drugs, the test should be repeated. This category implies possible clinical applicability in body sites where the drug is physiologically concentrated or in situations where high dosage of drug can be used. This category also provides a buffer zone which prevents small uncontrolled technical factors from causing major discrepancies in interpretation. A report of "Resistant" indicates that the pathogen is not likely to be inhibited if the antimicrobial compound in the blood reaches the concentrations usually achievable; other therapy should be selected.

Standardized susceptibility test procedures require the use of laboratory control microorganisms to control the technical aspects of the laboratory procedures. Standard erythromycin powder should provide the following MIC values:

Microorganism | MIC (µg/mL)
S. aureus ATCC 29213 | 0.12-0.5
E. faecalis ATCC 29212 | 1-4

Diffusion Techniques

Quantitative methods that require measurement of zone diameters also provide reproducible estimates of the susceptibility of bacteria to antimicrobial compounds. One such standardized procedure^2 requires the use of standardized inoculum concentrations. This procedure uses paper disks impregnated with 15-µg erythromycin to test the susceptibility of microorganisms to erythromycin.

Reports from the laboratory providing results of the standard single-disk susceptibility test with a 15-µg erythromycin disk should be interpreted according to the following criteria:

Zone Diameter (mm) | Interpretation
≥ 23 | Susceptible (S)
14-22 | Intermediate (I)
≤ 13 | Resistant (R)

Interpretation should be as stated above for results using dilution techniques. Interpretation involves correlation of the diameter obtained in the disk test with the MIC for erythromycin.

As with standardized dilution techniques, diffusion methods require the use of laboratory control microorganisms that are used to control the technical aspects of the laboratory procedures. For the diffusion technique, the 15-µg erythromycin disk should provide the following zone diameters in these laboratory test quality control strains:

Microorganism | Zone Diameter (mm)
S. aureus ATCC 25923 | 22-30

INDICATIONS AND USAGE

To reduce the development of drug-resistant bacteria and maintain the effectiveness of ERYTHROCIN STEARATE Filmtab tablets and other antibacterial drugs, ERYTHROCIN STEARATE Filmtab tablets should be used only to treat or prevent infections that are proven or strongly suspected to be caused by susceptible bacteria. When culture and susceptibility information are available, they should be considered in selecting or modifying antibacterial therapy. In the absence of such data, local epidemiology and susceptibility patterns may contribute to the empiric selection of therapy.

ERYTHROCIN STEARATE tablets are indicated in the treatment of infections caused by susceptible strains of the designated microorganisms in the diseases listed below:

Upper respiratory tract infections of mild to moderate degree caused by Streptococcus pyogenes; Streptococcus pneumoniae ; Haemophilus influenzae (when used concomitantly with adequate doses of sulfonamides, since many strains of H. influenzae are not susceptible to the erythromycin concentrations ordinarily achieved). (See appropriate sulfonamide labeling for prescribing information.)

Lower respiratory tract infections of mild to moderate severity caused by Streptococcus pyogenes or Streptococcus pneumoniae.

Listeriosis caused by Listeria monocytogenes.

Respiratory tract infections due to Mycoplasma pneumoniae.

Skin and skin structure infections of mild to moderate severity caused by Streptococcus pyogenes or Staphylococcus aureus (resistant staphylococci may emerge during treatment).

Pertussis (whooping cough) caused by Bordetella pertussis. Erythromycin is effective in eliminating the organism from the nasopharynx of infected individuals, rendering them noninfectious. Some clinical studies suggest that erythromycin may be helpful in the prophylaxis of pertussis in exposed susceptible individuals.

Diphtheria: Infections due to Corynebacterium diphtheriae, as an adjunct to antitoxin, to prevent establishment of carriers and to eradicate the organism in carriers.

Erythrasma: In the treatment of infections due to Corynebacterium minutissimum.

Intestinal amebiasis caused by Entamoeba histolytica (oral erythromycins only). Extraenteric amebiasis requires treatment with other agents.

Acute Pelvic Inflammatory Disease Caused by Neisseria gonorrhoeae: Erythrocin® Lactobionate-I.V. (erythromycin lactobionate for injection, USP) followed by erythromycin base orally, as an alternative drug in treatment of acute pelvic inflammatory disease caused by N. gonorrhoeae in female patients with a history of sensitivity to penicillin. Patients should have a serologic test for syphilis before receiving erythromycin as treatment of gonorrhea and a follow-up serologic test for syphilis after 3 months.

Erythromycins are Indicated for Treatment of the Following Infections Caused by Chlamydia trachomatis: Conjunctivitis of the newborn, pneumonia of infancy, and urogenital infections during pregnancy. When tetracyclines are contraindicated or not tolerated, erythromycin is indicated for the treatment of uncomplicated urethral, endocervical, or rectal infections in adults due to Chlamydia trachomatis.

When tetracyclines are contraindicated or not tolerated, erythromycin is indicated for the treatment of nongonococcal urethritis caused by Ureaplasma urealyticum.

Primary syphilis caused by Treponema pallidum. Erythromycin (oral forms only) is an alternative choice of treatment for primary syphilis in patients allergic to the penicillins. In treatment of primary syphilis, spinal fluid should be examined before treatment and as part of the follow-up after therapy.

Legionnaires' Disease caused by Legionella pneumophila. Although no controlled clinical efficacy studies have been conducted, in vitro and limited preliminary clinical data suggest that erythromycin may be effective in treating Legionnaires' Disease.

Prophylaxis

Prevention of Initial Attacks of Rheumatic Fever

Penicillin is considered by the American Heart Association to be the drug of choice in the prevention of initial attacks of rheumatic fever (treatment of Streptococcus pyogenes infections of the upper respiratory tract e.g., tonsillitis, or pharyngitis).^3 Erythromycin is indicated for the treatment of penicillin-allergic patients. The therapeutic dose should be administered for ten days.

Prevention of Recurrent Attacks of Rheumatic Fever

Penicillin or sulfonamides are considered by the American Heart Association to be the drugs of choice in the prevention of recurrent attacks of rheumatic fever. In patients who are allergic to penicillin and sulfonamides, oral erythromycin is recommended by the American Heart Association in the long-term prophylaxis of streptococcal pharyngitis (for the prevention of recurrent attacks of rheumatic fever).^3

CONTRAINDICATIONS

Erythromycin is contraindicated in patients with known hypersensitivity to this antibiotic.

Erythromycin is contraindicated in patients taking terfenadine, astemizole, pimozide or cisapride. (See PRECAUTIONS - Drug Interactions.)

WARNINGS

There have been reports of hepatic dysfunction, including increased liver enzymes, and hepatocellular and/or cholestatic hepatitis, with or without jaundice, occurring in patients receiving oral erythromycin products.

There have been reports suggesting that erythromycin does not reach the fetus in adequate concentration to prevent congenital syphilis. Infants born to women treated during pregnancy with oral erythromycin for early syphilis should be treated with an appropriate penicillin regimen.

Clostridium difficile associated diarrhea (CDAD) has been reported with use of nearly all antibacterial agents, including ERYTHROCIN® STEARATE Filmtab® Tablets, and may range in severity from mild diarrhea to fatal colitis. Treatment with antibacterial agents alters the normal flora of the colon leading to overgrowth of C. difficile.

C. difficile produces toxins A and B which contribute to the development of CDAD. Hypertoxin producing strains of C. difficile cause increased morbidity and mortality, as these infections can be refractory to antimicrobial therapy and may require colectomy. CDAD must be considered in all patients who present with diarrhea following antibiotic use. Careful medical history is necessary since CDAD has been reported to occur over two months after the administration of antibacterial agents.

If CDAD is suspected or confirmed, ongoing antibiotic use not directed against C. difficile may need to be discontinued. Appropriate fluid and electrolyte management, protein supplementation, antibiotic treatment of C. difficile, and surgical evaluation should be instituted as clinically indicated.

Rhabdomyolysis with or without renal impairment has been reported in seriously ill patients receiving erythromycin concomitantly with lovastatin. Therefore, patients receiving concomitant lovastatin and erythromycin should be carefully monitored for creatine kinase (CK) and serum transaminase levels. (See package insert for lovastatin.)

PRECAUTIONS

General

Prescribing ERYTHROCIN STEARATE Filmtab tablets in the absence of a proven or strongly suspected bacterial infection or a prophylactic indication is unlikely to provide benefit to the patient and increases the risk of the development of drug-resistant bacteria.

Since erythromycin is principally excreted by the liver, caution should be exercised when erythromycin is administered to patients with impaired hepatic function. (See CLINICAL PHARMACOLOGY and WARNINGS.)

Exacerbation of symptoms of myasthenia gravis and new onset of symptoms of myasthenic syndrome have been reported in patients receiving erythromycin therapy.

There have been reports of infantile hypertrophic pyloric stenosis (IHPS) occurring in infants following erythromycin therapy. In one cohort of 157 newborns who were given erythromycin for pertussis prophylaxis, seven neonates (5%) developed symptoms of non-bilious vomiting or irritability with feeding and were subsequently diagnosed as having IHPS requiring surgical pyloromyotomy. A possible dose-response effect was described with an absolute risk of IHPS of 5.1% for infants who took erythromycin for 8-14 days and 10% for infants who took erythromycin for 15-21 days.^4 Since erythromycin may be used in the treatment of conditions in infants which are associated with significant mortality or morbidity (such as pertussis or neonatal Chlamydia trachomatis infections), the benefit of erythromycin therapy needs to be weighed against the potential risk of developing IHPS. Parents should be informed to contact their physician if vomiting or irritability with feeding occurs.

Prolonged or repeated use of erythromycin may result in an overgrowth of nonsusceptible bacteria or fungi. If superinfection occurs, erythromycin should be discontinued and appropriate therapy instituted.

When indicated, incision and drainage or other surgical procedures should be performed in conjunction with antibiotic therapy.

Information for Patients

Patients should be counseled that antibacterial drugs including ERYTHROCIN STEARATE Filmtab tablets should only be used to treat bacterial infections. They do not treat viral infections (e.g., the common cold). When ERYTHROCIN STEARATE Filmtab tablets are prescribed to treat a bacterial infection, patients should be told that although it is common to feel better early in the course of therapy, the medication should be taken exactly as directed. Skipping doses or not completing the full course of therapy may (1) decrease the effectiveness of the immediate treatment and (2) increase the likelihood that bacteria will develop resistance and will not be treatable by ERYTHROCIN STEARATE Filmtab tablets or other antibacterial drugs in the future.

Diarrhea is a common problem caused by antibiotics which usually ends when the antibiotic is discontinued. Sometimes after starting treatment with antibiotics, patients can develop watery and bloody stools (with or without stomach cramps and fever) even as late as two or more months after having taken the last dose of the antibiotic. If this occurs, patients should contact their physician as soon as possible.

Drug Interactions

Erythromycin use in patients who are receiving high doses of theophylline may be associated with an increase in serum theophylline levels and potential theophylline toxicity. In case of theophylline toxicity and/or elevated serum theophylline levels, the dose of theophylline should be reduced while the patient is receiving concomitant erythromycin therapy.

Hypotension, bradyarrhythmias, and lactic acidosis have been observed in patients receiving concurrent verapamil, belonging to the calcium channel blockers drug class.

Concomitant administration of erythromycin and digoxin has been reported to result in elevated digoxin serum levels.

There have been reports of increased anticoagulant effects when erythromycin and oral anticoagulants were used concomitantly. Increased anticoagulation effects due to interactions of erythromycin with oral anticoagulants may be more pronounced in the elderly.

Erythromycin is a substrate and inhibitor of the 3A isoform subfamily of the cytochrome p450 enzyme system (CYP3A). Coadministration of erythromycin and a drug primarily metabolized by CYP3A may be associated with elevations in drug concentrations that could increase or prolong both the therapeutic and adverse effects of the concomitant drug. Dosage adjustments may be considered, and when possible, serum concentrations of drugs primarily metabolized by CYP3A should be monitored closely in patients concurrently receiving erythromycin.

The following are examples of some clinically significant CYP3A based drug interactions. Interactions with other drugs metabolized by the CYP3A isoform are also possible. The following CYP3A based drug interactions have been observed with erythromycin products in post-marketing experience:

Ergotamine/dihydroergotamine

Concurrent use of erythromycin and ergotamine or dihydroergotamine has been associated in some patients with acute ergot toxicity characterized by severe peripheral vasospasm and dysesthesia.

Triazolobenzodiazepines (Such as triazolam and alprazolam) and Related Benzodiazepines

Erythromycin has been reported to decrease the clearance of triazolam and midazolam, and thus, may increase the pharmacologic effect of these benzodiazepines.

HMG-CoA Reductase Inhibitors

Erythromycin has been reported to increase concentrations of HMG-CoA reductase inhibitors (e.g., lovastatin and simvastatin). Rare reports of rhabdomyolysis have been reported in patients taking these drugs concomitantly.

Sildenafil (Viagra)

Erythromycin has been reported to increase the systemic exposure (AUC) of sildenafil. Reduction of sildenafil dosage should be considered. (See Viagra package insert.)

There have been spontaneous or published reports of CYP3A based interactions of erythromycin with cyclosporine, carbamazepine, tacrolimus, alfentanil, disopyramide, rifabutin, quinidine, methylprednisolone, cilostazol, vinblastine, and bromocriptine.

Concomitant administration of erythromycin with cisapride, pimozide, astemizole, or terfenadine is contraindicated. (See CONTRAINDICATIONS.)

In addition, there have been reports of interactions of erythromycin with drugs not thought to be metabolized by CYP3A, including hexobarbital, phenytoin, and valproate.

Erythromycin has been reported to significantly alter the metabolism of the nonsedating antihistamines terfenadine and astemizole when taken concomitantly. Rare cases of serious cardiovascular adverse events, including electrocardiographic QT/QTc interval prolongation, cardiac arrest, torsades de pointes, and other ventricular arrhythmias, have been observed. (See CONTRAINDICATIONS.) In addition, deaths have been reported rarely with concomitant administration of terfenadine and erythromycin.

There have been post-marketing reports of drug interactions when erythromycin was co-administered with cisapride, resulting in QT prolongation, cardiac arrhythmias, ventricular tachycardia, ventricular fibrillation, and torsades de pointes, most likely due to the inhibition of hepatic metabolism of cisapride by erythromycin. Fatalities have been reported. (See CONTRAINDICATIONS).

Drug/Laboratory Test Interactions

Erythromycin interferes with the fluorometric determination of urinary catecholamines.

Carcinogenesis, Mutagenesis, Impairment of Fertility

Long-term (2-year) oral studies conducted in rats with erythromycin base did not provide evidence of tumorigenicity. Mutagenicity studies have not been conducted. There was no apparent effect on male or female fertility in rats fed erythromycin (base) at levels up to 0.25 percent of diet.

Pregnancy

Teratogenic effects

Pregnancy Category B

There is no evidence of teratogenicity or any other adverse effect on reproduction in female rats fed erythromycin base (up to 0.25 percent of diet) prior to and during mating, during gestation, and through weaning of two successive litters. There are, however, no adequate and well-controlled studies in pregnant women. Because animal reproduction studies are not always predictive of human response, this drug should be used during pregnancy only if clearly needed.

Labor and Delivery

The effect of erythromycin on labor and delivery is unknown.

Nursing Mothers

Erythromycin is excreted in human milk. Caution should be exercised when erythromycin is administered to a nursing woman.

Pediatric Use

See INDICATIONS AND USAGE and DOSAGE AND ADMINISTRATION.

Geriatric Use

Elderly patients, particularly those with reduced renal or hepatic function, may be at increased risk for developing erythromycin-induced hearing loss. (See ADVERSE REACTIONS and DOSAGE AND ADMINISTRATION).

Elderly patients may be more susceptible to the development of torsades de pointes arrhythmias than younger patients. (See ADVERSE REACTIONS).

Elderly patients may experience increased effects of oral anticoagulant therapy while undergoing treatment with erythromycin. (See PRECAUTIONS - Drug Interactions).

Erythrocin Stearate Filmtab ® Tablets (250 mg) contain 56.7 mg (2.5 mEq) of sodium and 5.0 mg (0.1 mEq) of potassium per tablet.

Erythrocin Stearate Filmtab ® Tablets (500 mg) contain no sodium and 7.0 mg (0.2 mEq) of potassium per tablet.

The geriatric population may respond with a blunted natriuresis to salt loading. This may be clinically important with regard to such diseases as congestive heart failure.

ADVERSE REACTIONS

The most frequent side effects of oral erythromycin preparations are gastrointestinal and are dose-related. They include nausea, vomiting, abdominal pain, diarrhea and anorexia. Symptoms of hepatitis, hepatic dysfunction and/or abnormal liver function test results may occur. (See WARNINGS.)

Onset of pseudomembranous colitis symptoms may occur during or after antibacterial treatment. (See WARNINGS.)

Erythromycin has been associated with QT prolongation and ventricular arrhythmias, including ventricular tachycardia and torsades de pointes.

Allergic reactions ranging from urticaria to anaphylaxis have occurred. Skin reactions ranging from mild eruptions to erythema multiforme, Stevens-Johnson syndrome, and toxic epidermal necrolysis have been reported rarely.

There have been rare reports of pancreatitis and convulsions.

There have been isolated reports of reversible hearing loss occurring chiefly in patients with renal insufficiency and in patients receiving high doses of erythromycin.

OVERDOSAGE

In case of overdosage, erythromycin should be discontinued. Overdosage should be handled with the prompt elimination of unabsorbed drug and all other appropriate measures should be instituted.

Erythromycin is not removed by peritoneal dialysis or hemodialysis.

DOSAGE AND ADMINISTRATION

Optimal serum levels of erythromycin are reached when ERYTHROCIN STEARATE (erythromycin stearate) is taken in the fasting state or immediately before meals.

Adults

The usual dosage is 250 mg every 6 hours; or 500 mg every 12 hours. Dosage may be increased up to 4 g per day according to the severity of the infection. However, twice-a-day dosing is not recommended when doses larger than 1 g daily are administered.

Children

Age, weight, and severity of the infection are important factors in determining the proper dosage. The usual dosage is 30 to 50 mg/kg/day, in equally divided doses. For more severe infections this dosage may be doubled but should not exceed 4 g per day.

In the treatment of streptococcal infections of the upper respiratory tract (e.g., tonsillitis or pharyngitis), the therapeutic dosage of erythromycin should be administered for at least ten days.

The American Heart Association suggests a dosage of 250 mg of erythromycin orally, twice a day in long-term prophylaxis of streptococcal upper respiratory tract infections for the prevention of recurring attacks of rheumatic fever in patients allergic to penicillin and sulfonamides.^3

Conjunctivitis of the Newborn Caused by Chlamydia trachomatis

Oral erythromycin suspension 50 mg/kg/day in 4 divided doses for at least 2 weeks.^3

Pneumonia of Infancy Caused by Chlamydia trachomatis

Although the optimal duration of therapy has not been established, the recommended therapy is oral erythromycin suspension 50 mg/kg/day in 4 divided doses for at least 3 weeks.

Urogenital Infections During Pregnancy Due to Chlamydia trachomatis

Although the optimal dose and duration of therapy have not been established, the suggested treatment is 500 mg of erythromycin by mouth four times a day or two erythromycin 333 mg tablets orally every 8 hours on an empty stomach for at least 7 days. For women who cannot tolerate this regimen, a decreased dose of one erythromycin 500 mg tablet orally every 12 hours, one 333 mg tablet orally every 8 hours or 250 mg by mouth four times a day should be used for at least 14 days.^5

For Adults With Uncomplicated Urethral, Endocervical, or Rectal Infections Caused by Chlamydia trachomatis, When Tetracycline is Contraindicated or Not Tolerated

500 mg of erythromycin by mouth four times a day or two 333 mg tablets orally every 8 hours for at least 7 days.^5

For Patients With Nongonococcal Urethritis Caused by Ureaplasma urealyticum When Tetracycline is Contraindicated or Not Tolerated

500 mg of erythromycin by mouth four times a day or two 333 mg tablets orally every 8 hours for at least seven days.^5

Primary Syphilis

30 to 40 g given in divided doses over a period of 10 to 15 days.

Acute Pelvic Inflammatory Disease Caused by N. gonorrhoeae

500 mg Erythrocin Lactobionate-I.V. (erythromycin lactobionate for injection, USP) every 6 hours for 3 days, followed by 500 mg of erythromycin base orally every 12 hours, or 333 mg of erythromycin base orally every 8 hours for 7 days.

Intestinal Amebiasis

Adults

500 mg every 12 hours, 333 mg every 8 hours or 250 mg every 6 hours for 10 to 14 days.

Children

30 to 50 mg/kg/day in divided doses for 10 to 14 days.

Pertussis

Although optimal dosage and duration have not been established, doses of erythromycin utilized in reported clinical studies were 40 to 50 mg/kg/day, given in divided doses for 5 to 14 days.

Legionnaires' Disease

Although optimal dosage has not been established, doses utilized in reported clinical data were 1 to 4 g daily in divided doses.

HOW SUPPLIED

ERYTHROCIN STEARATE Filmtab Tablets (erythromycin stearate tablets, USP) are supplied in the following strengths and packages.

ERYTHROCIN STEARATE Filmtab, 250 mg pink tablets imprinted with the corporate Abbott “A” logo and the Abbo-Code designation ES:

Bottles of 100…...…………………………………………………..(NDC 0074-6346-20)

Bottles of 500…...…………………………………………………..(NDC 0074-6346-53)

ERYTHROCIN STEARATE Filmtab, 500 mg pink tablets imprinted with the corporate Abbott “A” logo and the Abbo-Code designation ET:

Bottles of 100……………………………………………………….(NDC 0074-6316-13)

Recommended Storage

Store below 86°F (30°C).

REFERENCES

1. National Committee for Clinical Laboratory Standards. Methods for Dilution Antimicrobial Susceptibility Tests for Bacteria that Grow Aerobically , Third Edition. Approved Standard NCCLS Document M7-A3, Vol. 13, No. 25 NCCLS, Villanova , PA, December 1993.
2. National Committee for Clinical Laboratory Standards, Performance Standards for Antimicrobial Disk Susceptibility Tests, Fifth Edition. Approved Standard NCCLS Document M2-A5, Vol. 13, No. 24 NCCLS, Villanova , PA, December 1993.
3. Committee on Rheumatic Fever, Endocarditis, and Kawasaki Disease of the Council on Cardiovascular Disease in the Young, the American Heart Association: Prevention of Rheumatic Fever. Circulation. 78(4):1082-1086, October 1988.
4. Honein, M.A., et. al.: Infantile hypertrophic pyloric stenosis after pertussis prophylaxis with erythromycin: a case review and cohort study. The Lancet 1999;354 (9196):2101-5.
5. Data on file, Abbott Laboratories.

FILMTAB-Film-sealed tablets, Abbott.

Abbott Laboratories

North Chicago, IL 60064, U.S.A.

Principal Display Panel

Erythrocin® Stearate Filmtab® (Erythromycin Stearate Tablets, USP) 250mg
28 Tablets
NDC 10544-594-28

Principal Display Panel

Erythrocin® Stearate Filmtab® (Erythromycin Stearate Tablets, USP) 500mg
28 Tablets
NDC 10544-595-28